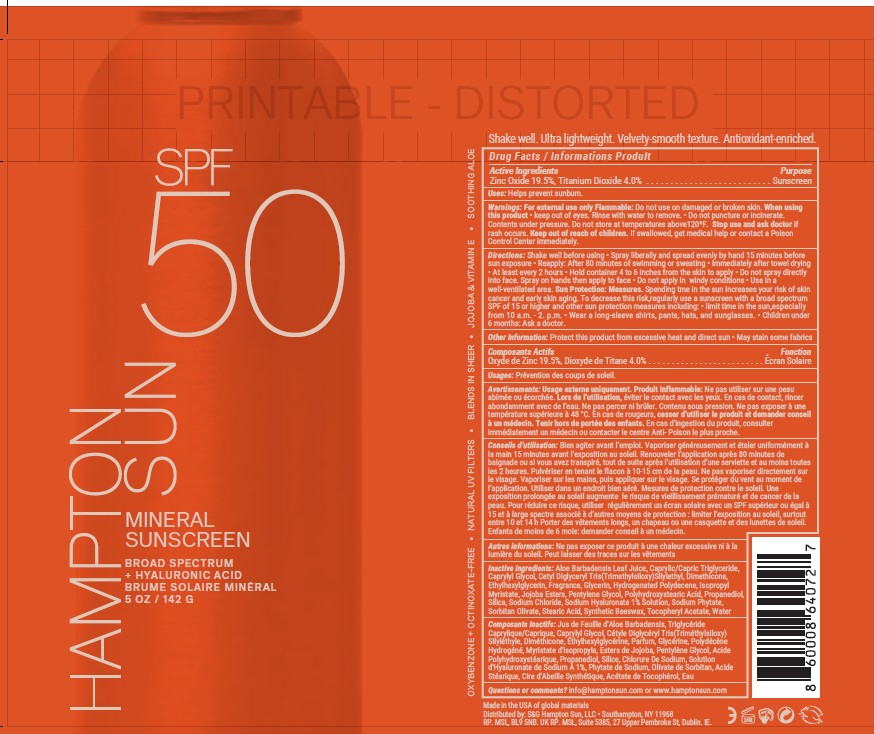 DRUG LABEL: Hampton Sun SPF 50 Mineral
NDC: 87170-011 | Form: SPRAY
Manufacturer: S&C Hampton Sun LLC
Category: otc | Type: HUMAN OTC DRUG LABEL
Date: 20260206

ACTIVE INGREDIENTS: ZINC OXIDE 19.5 g/100 g; TITANIUM DIOXIDE 4 g/100 g
INACTIVE INGREDIENTS: ALOE; CAPRYLYL GLYCOL; CETYL DIGLYCERYL TRIS(TRIMETHYLSILOXY)SILYLETHYL DIMETHICONE (950 MM2/S); ETHYLHEXYLGLYCERIN; FRAGRANCE LY-11285; GLYCERIN; ISOPROPYL MYRISTATE; PENTYLENE GLYCOL; PROPANEDIOL; SILICA; SODIUM CHLORIDE; SODIUM HYALURONATE; SODIUM PHYTATE; SORBITAN OLIVATE; SYNTHETIC BEESWAX; .ALPHA.-TOCOPHEROL ACETATE, DL-; WATER

Hampton Sun SFP 50 Mineral Spray (IS0265-HS)

Actove Ingredeints Purpose

Zinc Oxide 19.5% Sunscreen

Titanium Dioxide 4% Sunscreen

Uses

Uses ■ helps prevent sunburn

DOSAGE AND ADMINISTRATION

Directionsapply liberally to cool, dry skin
15 minutes before sun exposure • reapply:
• after 80 minutes of swimming or sweating
• immediately after towel drying • at least every 2
hours • Sun Protection Measures. Spending time
in the sun increases your risk of skin cancer and
early skin aging. To decrease this risk, regularly
use a sunscreen with a broad spectrum SPF of 15
or higher and other sun protection measures
including: • limit time in the sun,especially from
10 a.m. - 2. p.m. • wear a long-sleeve shirts,
pants, hats, and sunglasses. • children under 6
months: Ask a doctor.
■ do not spray
directly Into face. Spray on hands then apply to face ■ use In
well-ventilated area.
Hold container 6-8 inches from the skin to apply

Warnings

For external use only.
Flammable: Do not use white smoking or near heat or flame.
Do not useon damaged or broken skin.
When using this product■ keep out of eyes. Rinse eyes with water
to remove.
Stop use and ask a doctor ifrash occurs.

Keep out of reach of children.if swallowed, get medical
help or contact a Polson Control Center right away.

Inactive Ingredients

Aloe Barbadensis Leaf Juice
Caprylic/Capric Triglyceride
Caprylyl Glycol
Cetyl Diglyceryl Tris(Trimethylsiloxy)silylethyl Dimethicone
Dimethicone
Ethylhexylglycerin
Fragrance
Glycerin
Hydrogen Dimethicone
Isopropyl Myristate
Jojoba Esters
Pentylene Glycol
Polyhydroxystearic Acid
Propanediol
Silica
Sodium Chloride
Sodium Hyaluronate
Sodium Phytate
Sorbitan Olivate
Stearic Acid
Synthetic Beeswax
Tocopheryl Acetate
Water